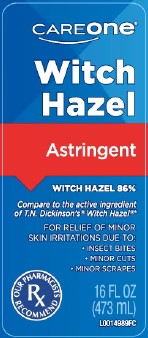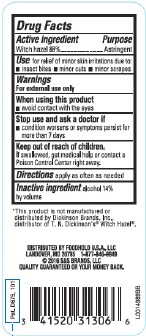 DRUG LABEL: Witch Hazel
NDC: 41520-822 | Form: LIQUID
Manufacturer: American Sales Company
Category: otc | Type: HUMAN OTC DRUG LABEL
Date: 20260206

ACTIVE INGREDIENTS: WITCH HAZEL 860 mg/1 mL
INACTIVE INGREDIENTS: ALCOHOL

Care One 822.001/822AA
Witch Hazel

Active ingredient

Witch Hazel 86%

Purpose

Astringent

Uses

for relief of minor skin irritations due to:

- insect bites
- minor cuts
- minor scrapes

Warnings

For external use only

When using this product

avoid contact with the eyes

Stop use and ask a doctor if

- condition worsens or symptoms persist for more than 7 days

Keep out of reach of children.

If swallowed, get medical help or contact a Poison Control Center right away.

Directions

apply as often as needed

Inactive ingredient

alcohol 14% by volume

Disclaimer

*This product is not manufactured or distributed by Dickinson Brands, Inc., distributor of T. N. Dickinson's®Witch Hazel.

ADVERSE REACTION

DISTRIBUTED BY

FOODHOLD U.S.A., LLC

LANDOVER, MD 20785

1-877-846-9949

Quality Guaranteed or your money back.

Pat. D675, 101

Principal display panel

CAREONE®

WITCH HAZEL

ASTRINGENT

WITCH HAZEL 86%

Compare to the active ingredient of T. N. Dickinson's®Witch Hazel®*

For Relief of minor sin irritations due to:

- Insect bites
- Minor cuts
- Minor scrapes

OUR PHARMACISTS RECOMMEND

16 FL OZ (473 mL)